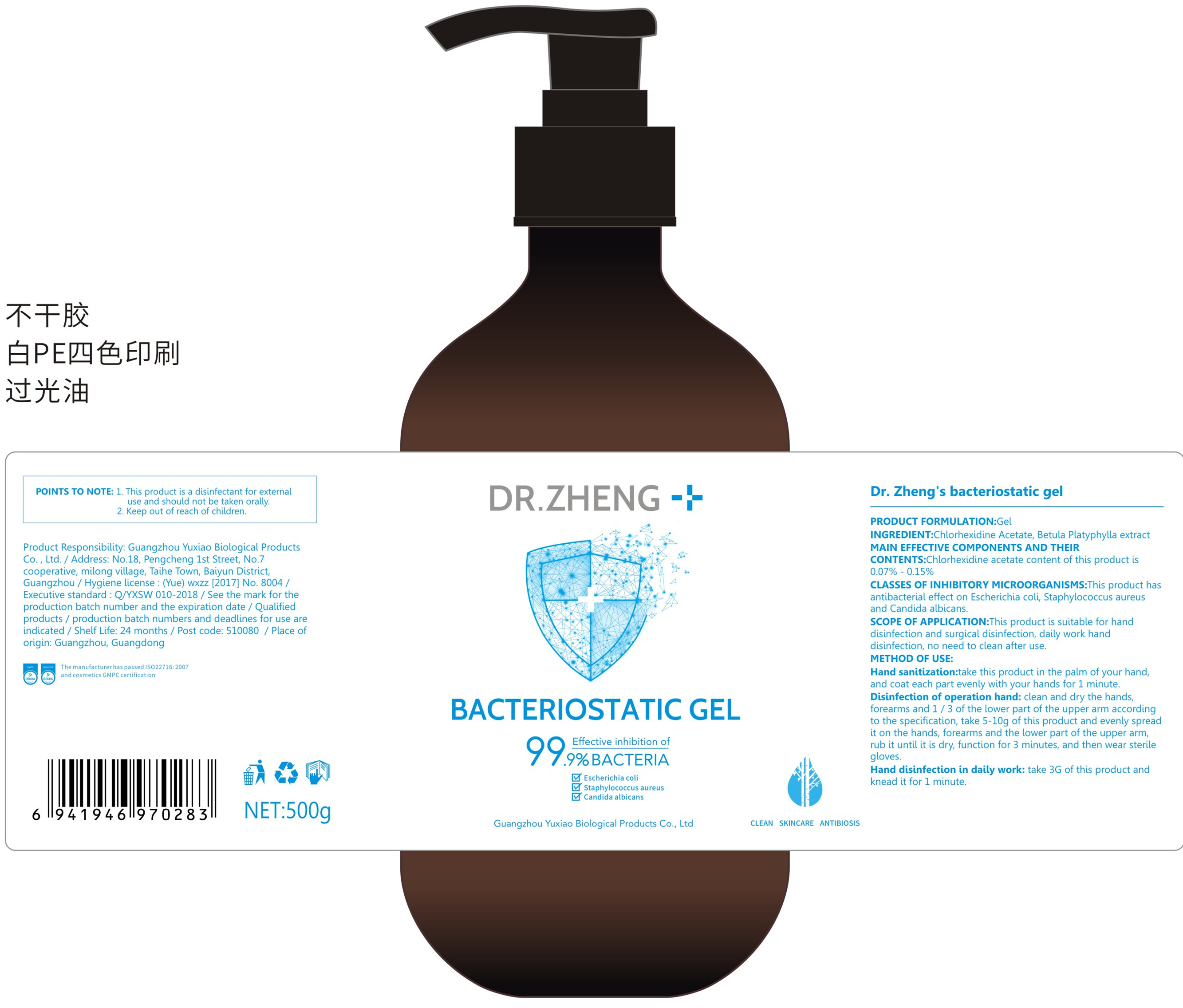 DRUG LABEL: Dr. Zheng s acteriostatic gel
NDC: 42091-002 | Form: GEL
Manufacturer: Guangzhou Yuxiao Biological Products Co., Ltd.
Category: otc | Type: HUMAN OTC DRUG LABEL
Date: 20200411

ACTIVE INGREDIENTS: CHLORHEXIDINE ACETATE 0.55 g/500 g
INACTIVE INGREDIENTS: BETULA PLATYPHYLLA BARK

DOSAGE AND ADMINISTRATION

Please store in a cool and dry place.

INACTIVE INGREDIENT

Betula platyphylla extract

INDICATIONS AND USAGE

Hand sanitization:take this product in the palm of your hand,and coat each part evenly with your hands for 1 minute.Disinfection of operation hand: clean and dry the hands,forearms and 1/ 3 of the lower part of the upper arm according to the specification, take 5-10g of this product and evenly spreadit on the hands, forearms and the lower part of the upper arm,rub it until it is dry, function for 3 minutes, and then wear sterilegloves.
Hand disinfection in daily work: take 3G of this product andknead it for 1 minute.

ACTIVE INGREDIENT

Chlorhexidine acetate

keep out of children

PURPOSE

Disinfection
Sterilization
No Rinseing

WARNINGS

1.This product is a disinfectant for external use and should not be taken orally.
2.Keep out of reach of children.